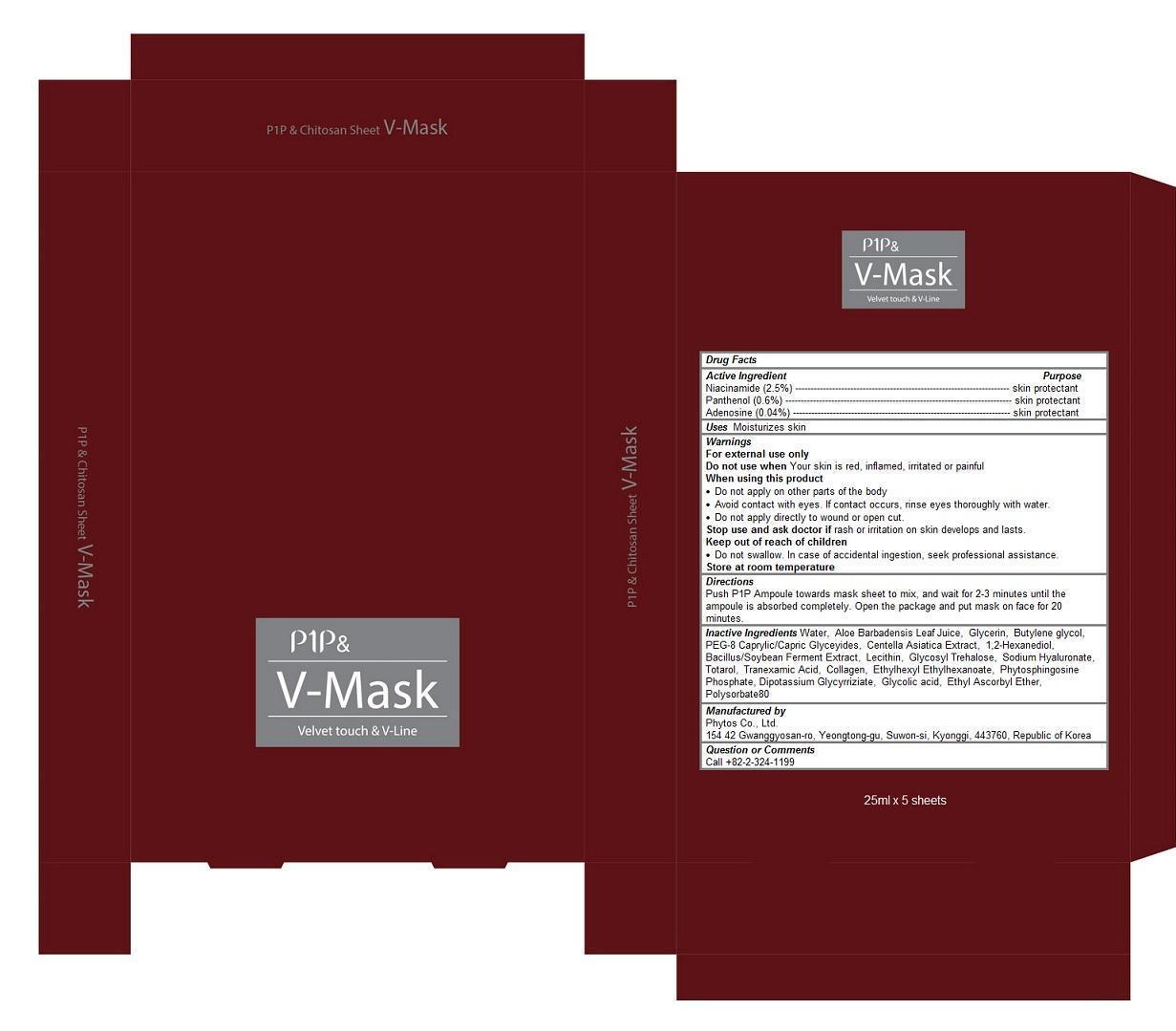 DRUG LABEL: P1P Chitosan V-mask
NDC: 69579-102 | Form: PATCH
Manufacturer: Phytos Co., Ltd.
Category: otc | Type: HUMAN OTC DRUG LABEL
Date: 20150128

ACTIVE INGREDIENTS: niacinamide 0.025 1/25 mL; adenosine 0.0004 1/25 mL; Panthenol 0.006 1/25 mL
INACTIVE INGREDIENTS: water; ALOE VERA LEAF; glycerin; BUTYLENE GLYCOL; PEG-8 CAPRYLIC/CAPRIC GLYCERIDES; CENTELLA ASIATICA; 1,2-HEXANEDIOL; EGG PHOSPHOLIPIDS; HYALURONATE SODIUM; TOTAROL; TRANEXAMIC ACID; COLLAGEN ALPHA-1(III) (HUMAN); ETHYLHEXYL ETHYLHEXANOATE; GLYCYRRHIZINATE DIPOTASSIUM; glycolic acid; polysorbate 80

P1P & Chitosan V-mask